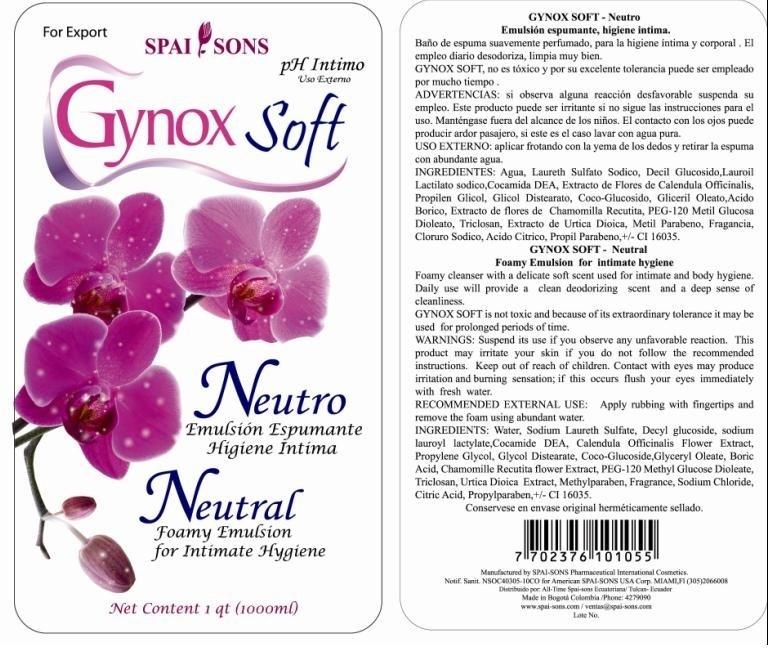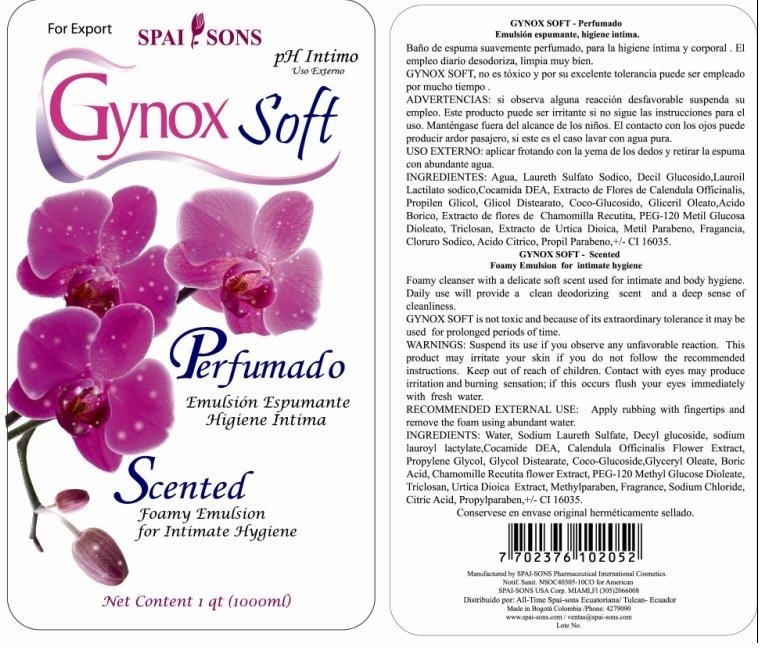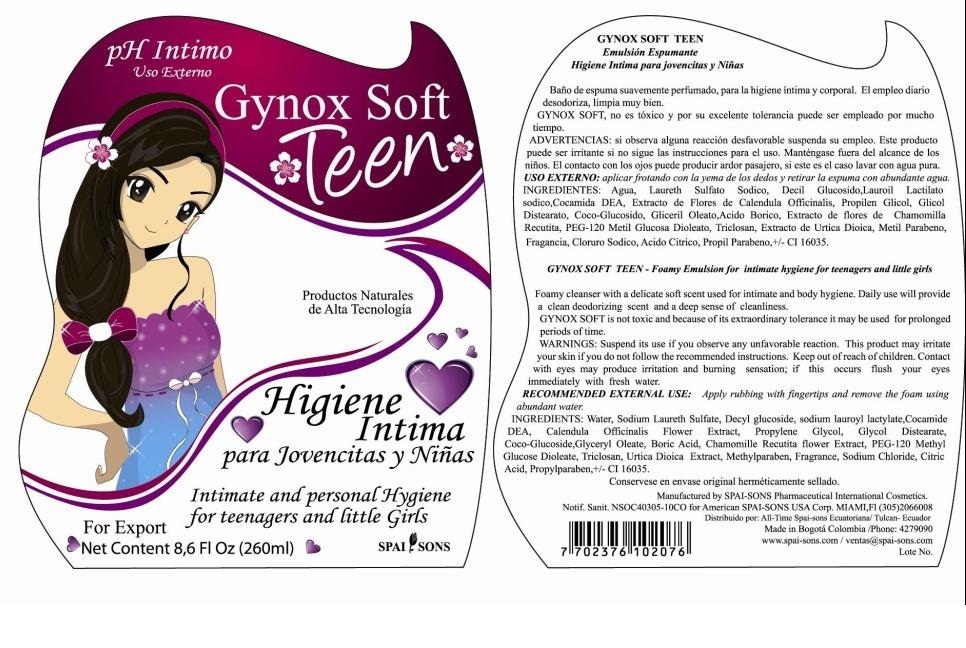 DRUG LABEL: GYNOX-SOFT
NDC: 66854-003 | Form: EMULSION
Manufacturer: SPAI-SONS PHARMACEUTICAL INTERNATIONAL COSMETICS
Category: otc | Type: HUMAN OTC DRUG LABEL
Date: 20120607

ACTIVE INGREDIENTS: BORIC ACID 7 mg/100 mL
INACTIVE INGREDIENTS: WATER; SODIUM LAURETH SULFATE; DECYL GLUCOSIDE; SODIUM LAUROYL LACTYLATE; COCO DIETHANOLAMIDE; CALENDULA OFFICINALIS FLOWER; PROPYLENE GLYCOL; GLYCOL DISTEARATE; COCO GLUCOSIDE; GLYCERYL OLEATE; CHAMOMILE; PEG-120 METHYL GLUCOSE DIOLEATE; FD&C RED NO. 40

GYNOX-SOFT NEUTRAL, SCENTED AND TEEN, Foamy emulsion for Intimate hygiene

ACTIVE INGREDIENT

GYNOX-SOFT is a foaming emulsion with Boric acid that is a antiseptic agent to control the microbial load present in the intimate area.

PURPOSE

GYNOX SOFT NEUTRAL, SCENTED OR TEEN, bubble bath is an antibacterial action, cleaning, fungicidal, and antibacterial that can be used by the whole family, including new borns.

KEEP OUT OF REACH OF CHILDREN

This product must be out of reach of children

INDICATIONS AND USAGE

GYNOX-SOFT is intimate hygiene foaming emulsion and body for men, women and teenagers of antibacterial action. Is pH balanced, is in daily use before, during and after the menstrual cycle, deep asepsis of hands skin complaints and scalp.

WARNINGS

Suspend its use if you observed any desfavorable reaction. This product may be irritate your skin if you do not follow the recommended instructions. Contact with eyes may produce irritation and burning sensation; if this occurs flush your eyes immediately with fresh water.

DOSAGE AND ADMINISTRATION

This product is for topical application. Add in the application area amount of product, rub gently to obtain foam and rinse.

INACTIVE INGREDIENT

This product is an emulsion, made with ingredients that provide moisturization, and protection in the intimate area. Is non toxic and has no known contraindications.

IMAGE OF THE LABEL